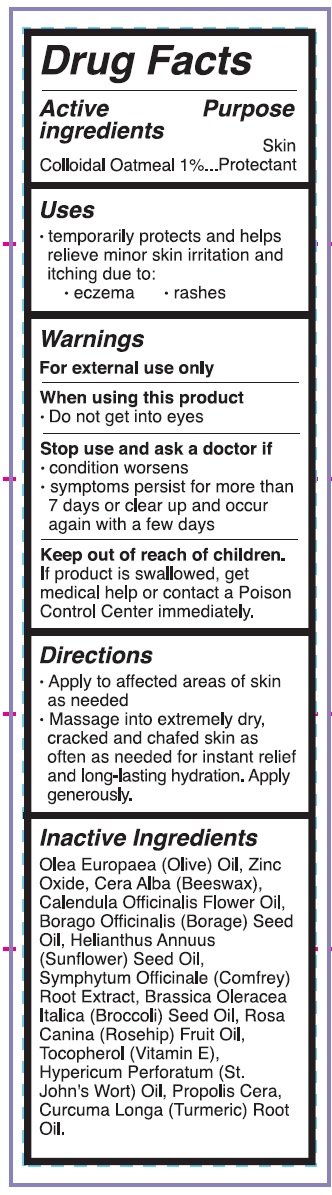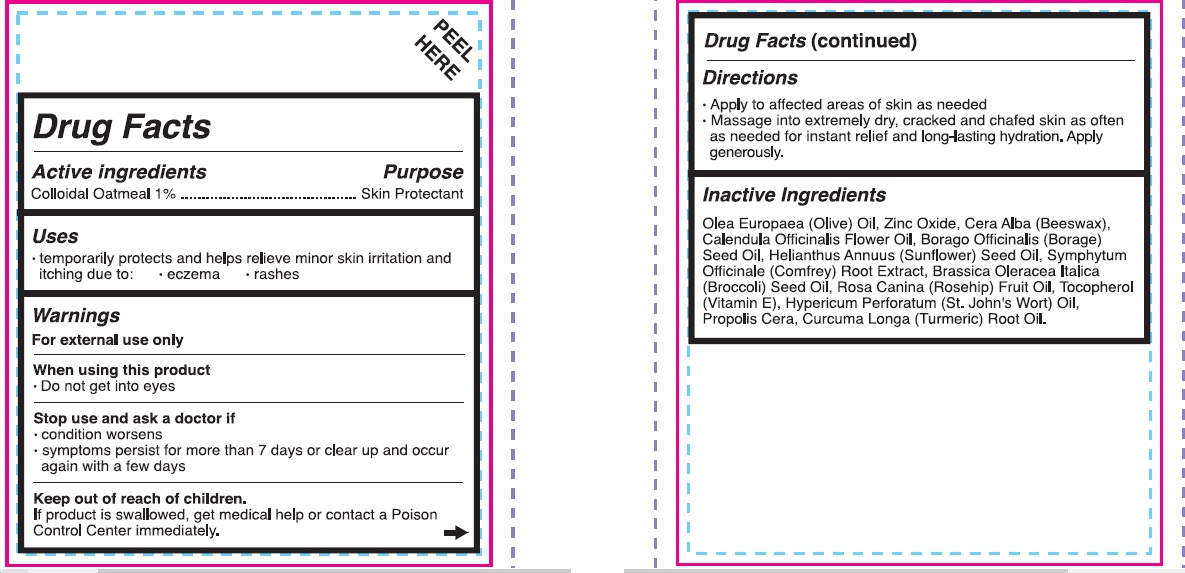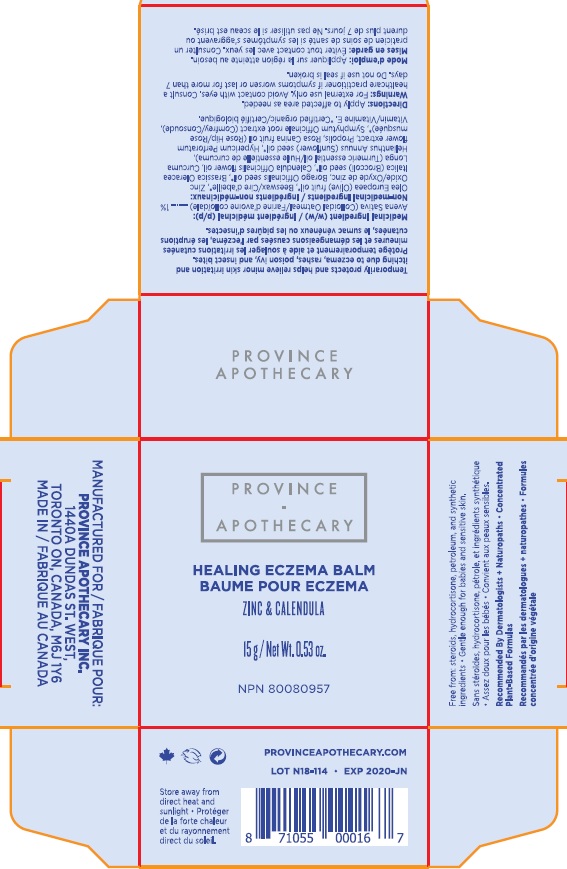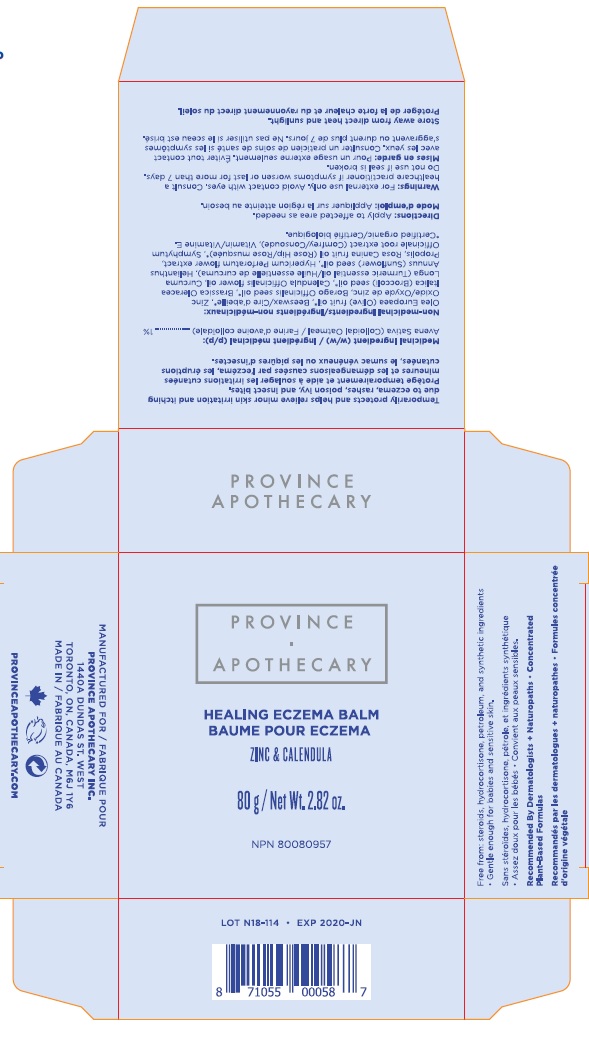 DRUG LABEL: HEALING ECZEMA BALM
NDC: 72257-001 | Form: CREAM
Manufacturer: PROVINCE APOTHECARY INC
Category: otc | Type: HUMAN OTC DRUG LABEL
Date: 20220101

ACTIVE INGREDIENTS: OATMEAL 1 g/100 g
INACTIVE INGREDIENTS: OLIVE OIL; ZINC OXIDE; YELLOW WAX; CALENDULA OFFICINALIS FLOWER; BORAGO OFFICINALIS SEED; SUNFLOWER OIL; COMFREY ROOT; BROCCOLI SEED OIL; ROSA CANINA FRUIT OIL; .ALPHA.-TOCOPHEROL; HYPERICUM PERFORATUM; PROPOLIS WAX; TURMERIC OIL

HEALING ECZEMA BALM 15G 80G

HEALING ECZEMA BALM

Drug Facts

Active Ingredients

- Colloidal Oatmeal 1 %

Purpose

Skin Protectant

Uses

- temporarily protects and helps relieve minor skin irritation and itching due to:
  - eczema
  - rashes

Warnings

- For external use only

When using this product

- Do not get into eyes.

Stop use and ask a doctor if

- condition worsens
  - symptoms persist for more than 7 days or clear up and occur again within a few days.

Keep out of reach of children.

- . If product is swallowed, get medical help or contact a Poison Control Center immediately.

Directions

- Apply to affected areas of skin as needed
- Massage into extremely dry, cracked and chafed skin as often as needed for instant relief and long-lasting hydration. Apply generously.

Inactive ingredients

- Olea Europaea (Olive) Oil, Zinc Oxide, Cera Alba (Beesawax), Calendula Officinalis Flower Oil, Borago Officinalis (Borage) Seed Oil, Helianthus Annuus (Sunflower) Seed Oil, Symphytum Officinale (Comfrey) Root Extract, Brassica Oleracea Italica (Broccoli) Seed Oul, Rosa Canina (Rosehip) Fruit Oil, Tocopherol (Vitamin E), Hypericum Perforatum (St.John's Wort) Oil, Propolis Cera, Curcuma Longa (Turmeric) Root Oil.